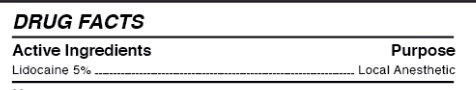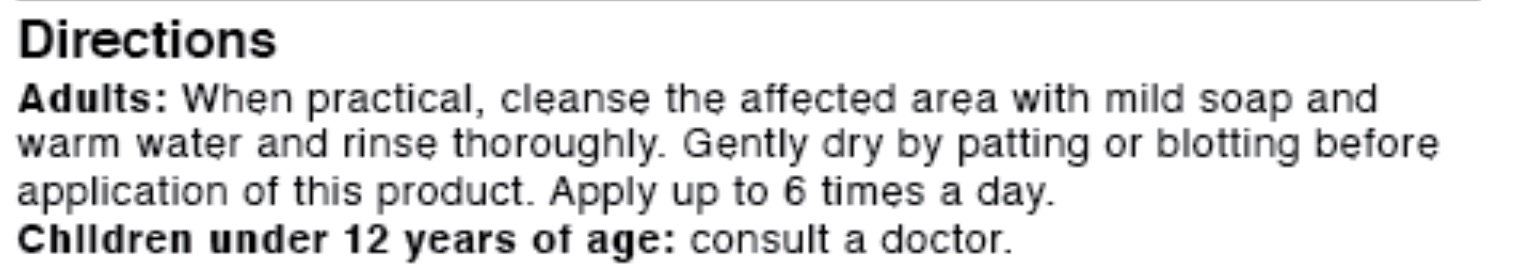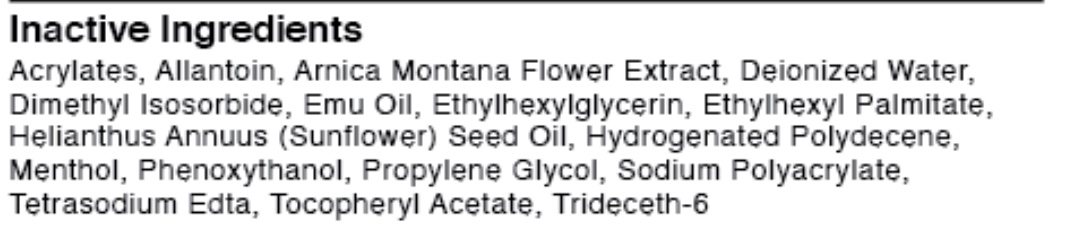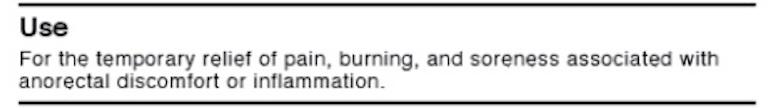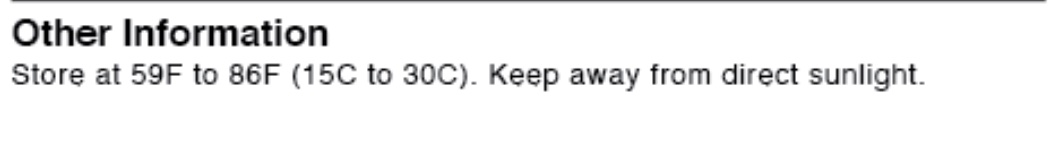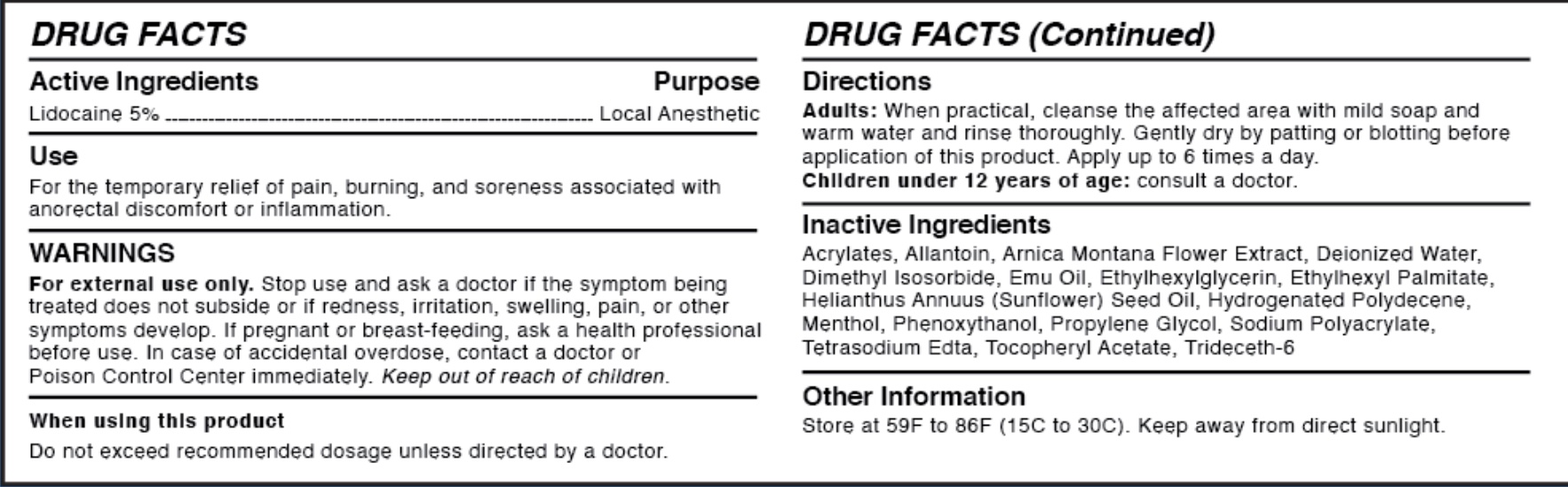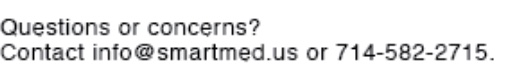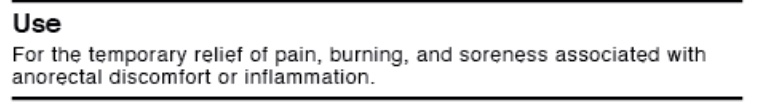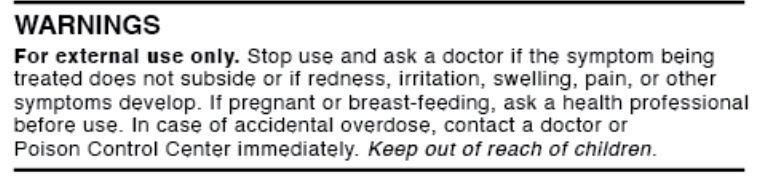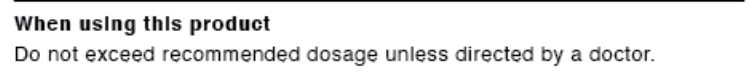 DRUG LABEL: SMART Numb Lidocaine Cream
NDC: 76092-201 | Form: CREAM
Manufacturer: M.J. Winston International, Ltd.
Category: otc | Type: HUMAN OTC DRUG LABEL
Date: 20250806

ACTIVE INGREDIENTS: LIDOCAINE 5 g/100 g
INACTIVE INGREDIENTS: PROPYLENE GLYCOL; ARNICA MONTANA FLOWER; MENTHOL; TRIDECETH-6; ETHYLHEXYLGLYCERIN; PHENOXYETHANOL; SUNFLOWER OIL; EDETATE SODIUM; SODIUM POLYACRYLATE (2500000 MW); HYDROGENATED POLYDECENE (1500 CST); WATER; DIMETHYL ISOSORBIDE; EMU OIL; ALLANTOIN; .ALPHA.-TOCOPHEROL ACETATE, D-; ETHYLHEXYL PALMITATE; ACRYLATES/C10-30 ALKYL ACRYLATE CROSSPOLYMER (60000 MPA.S)

WARNINGS

For external use only.

Stop use and ask a doctor if the symptom being treated does not subside or if redness, irritation, swelling, pain, or other symptoms develop. If pregnant or breast-feeding, ask a health professional before use.

In case of accidental overdose, contact a doctor or Poison Control Center immediately. Keep out of reach of children.

Active Ingredients

Lidocaine 5% local anesthetic

Use

For the temporary relief of pain, burning, and soreness associted with anorectal discomfort or inflammation.

When using this product

Do not excceed recommended dosage unless directed by a doctor.

Directions

Adults: When practical, cleanse the affected area with mild soap and warm water and rinse thoroughly. Gently dry by patting or blotting with toilet tissue or a soft cloth before application of this product. For products for external use only. Apply up to 6 times a day. Children under 12 years of age: consult a doctor.

Inactive Ingredients

Aacrylates, Allantoin, Arnice Montana Flower Extract, Deionized Water, Dimethyl Isosorbide, Emu Oil, Ethylhexyl Palmitate, Helianthus Annuus (Sunflower) Seed Oil, Hydrogenated Polydecene, Menthol, Phenoxythanol, Propylene Glycol, Sodium Polyacrylate, Tetrasodium Edta, Tocopheryl Acetate, Trideceth-6

Other Information

Store at 59F to 86F (15C to 30C). Keep away from direct sunlight.

Questions or concerns?

Contact info@smartmed.us or 714-582-2715.

Keep out of reach of children.

Use

For the temporary relief of pain, burning, and soreness associated with anorectal discomfort or inflammation.